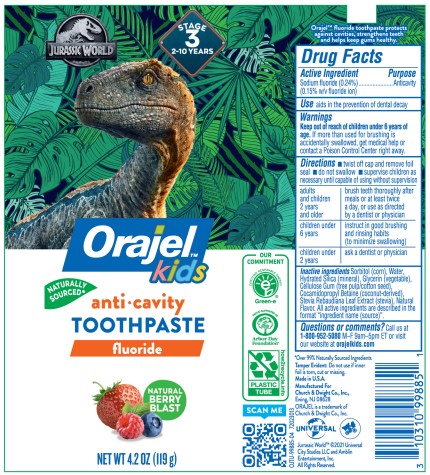 DRUG LABEL: Orajel
NDC: 10237-775 | Form: GEL, DENTIFRICE
Manufacturer: Church & Dwight Co., Inc.
Category: otc | Type: HUMAN OTC DRUG LABEL
Date: 20241127

ACTIVE INGREDIENTS: SODIUM FLUORIDE 1.5 mg/1 g
INACTIVE INGREDIENTS: SORBITOL; SODIUM LAURYL SULFATE; FD&C BLUE NO. 1; CARBOXYMETHYLCELLULOSE SODIUM; POLYETHYLENE GLYCOL 400; SACCHARIN SODIUM; HYDRATED SILICA; WATER

Orajel Anticavity Fluoride Toothpaste

ACTIVE INGREDIENT

Sodium Fluoride (0.24%)

(0.15% w/v fluoride ion)

PURPOSE

Anticavity

INDICATIONS AND USAGE

Aids in the prevention of dental decay

WARNINGS

If more than used for brushing is accidentally swallowed, get medical help or contact a Poison Control Center right away.

Keep out of reach of children under 6 years of age.

Directions

- twist off cap and remove foil seal
- do not swallow
- supervise children as necessary until capable of using without supervision

adults and children 2 years and older | brush teeth thoroughly after meals or at least twice a day, or use as directed by a dentist or physician
children under 6 years | instruct in good brushing and rinsing habits (to minimize swallowing)
children under 2 years | ask a denist or physician

INACTIVE INGREDIENT

Sorbitol (corn), Water, Hydrated Silica (mineral), Glycerin (vegetable), Cellulose Gum (tree pulp/cotton seed), Cocamidopropyl Betaine (coconut-derived), Stevia Rebaudiana Leaf Extract (stevia), Natural Flavor. All active ingredients are described in the format "ingredient name (source)".

QUESTIONS

Questions of comments? Call us at 1-800-952-5080 M-F 9am - 5pm ET or visit our website at orajelkids.com

PACKAGE LABEL

JURASSIC WORLD

Stage

3

2-10 YEARS

Orajel™

kids

NATURALLY

SOURCED*

anti•cavity

TOOTHPASTE

fluoride

NATURAL

BERRY

BLAST

OUR

COMMITMENT

CERTIFIED RENEWABLE ENERGY

Green-e®

PROUD SUPPORTER OF

Arbor Day

Foundation®

PLASTIC

TUBE

how2recycle.info

SCAN ME

NET WT 4.2 OZ (119 g)